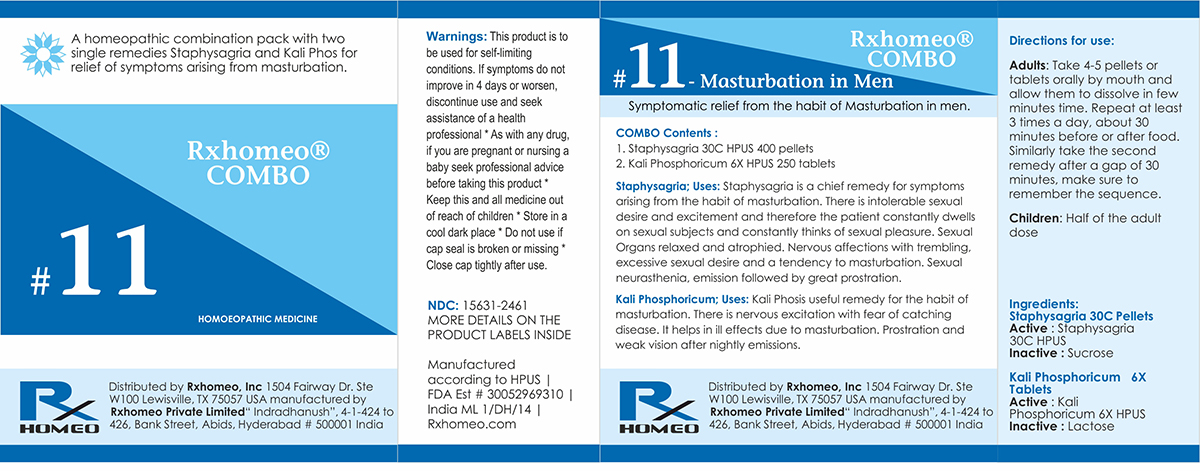 DRUG LABEL: Rxhomeo Homeopathic Combo 11
NDC: 15631-2461 | Form: KIT | Route: ORAL
Manufacturer: Rxhomeo Private Limited d.b.a.
Category: homeopathic | Type: HUMAN OTC DRUG LABEL
Date: 20161022

ACTIVE INGREDIENTS: DELPHINIUM STAPHISAGRIA SEED 3 [hp_X]/1 1; POTASSIUM PHOSPHATE, DIBASIC 1 [hp_X]/1 1
INACTIVE INGREDIENTS: SUCROSE; LACTOSE

ACTIVE INGREDIENT

STAPHYSAGRIA HPUS 3X and higher

KALI PHOSPHORICUM HPUS 1X and higher

USES

A homeopathic combination pack with two single remedies Staphysagria and Kali Phos for relief of symptoms arising from masturbation.

Staphysagria: Staphysagria is a chief remedy for symptoms arising from the habit of masturbation. There is intolerable sexual desire and excitement and therefore the patient constantly dwells on sexual subjects and constantly thinks of sexual pleasure. Sexual Organs relaxed and atrophied. Nervous affections with trembling, excessive sexual desire and a tendency to masturbation. Sexual neurasthenia, emission followed by great prostration.

Kali Phos: Kali Phos is useful remedy for the habit of masturbation. There is nervous excitation with fear of catching disease. It helps in ill effects due to masturbation. Prostration and weak vision after nightly emissions.

INDICATIONS

Condition listed above or as directed by the physician

DOSAGE

Adults: Take 4-5 pellets or tablets orally by mouth and allow them to dissolve on tongue. Repeat at least 3 times a day, about 30 minutes before or after food. Similarly take the second remedy after a gap of 30 minutes, make sure to remember the sequence.

Children: Half of the adult dose.

WARNINGS

This product is to be used for self-limiting conditions

STOP USE

If symptoms do not improve in 4 days, or worsen, discontinue use and seek assistance of health professional

KEEP OUT OF REACH OF CHILDREN

Keep this and all medication out of reach of children

Do not use if capseal is broken or missing.

Close the cap tightly after use.

INACTIVE INGREDIENTS

Sucrose for Pellets.

Lactose for Tablets.

STORAGE

Store in a cool dark place

QUESTIONS OR COMMENTS

www.Rxhomeo.com | 1.888.2796642 | info@rxhomeo.com
Rxhomeo, Inc 1504 Fairway Dr. Ste W 100 Lewisville, TX 75057 USA